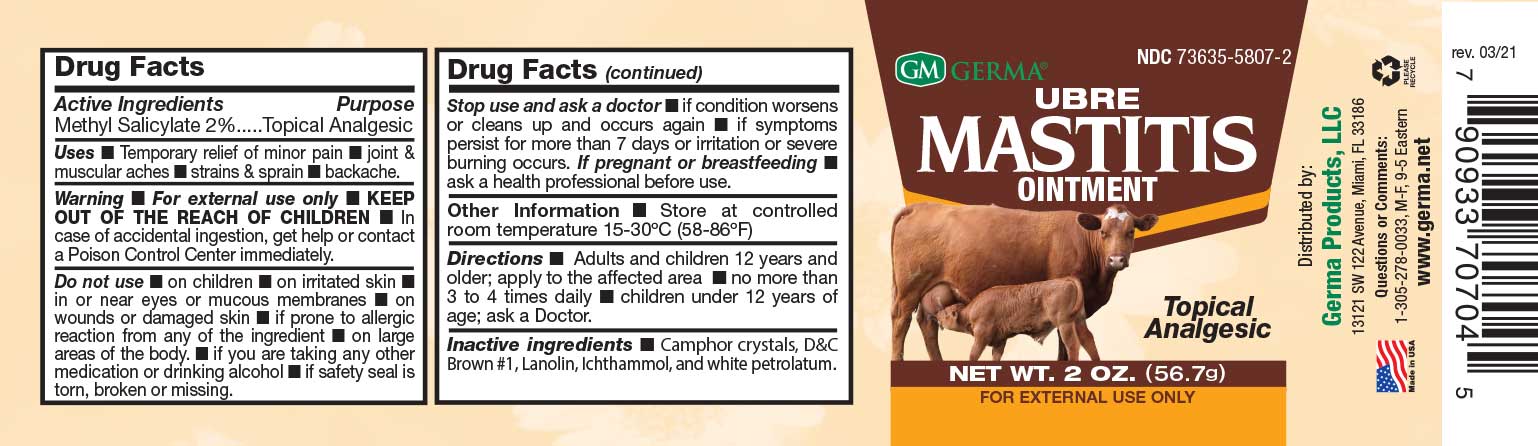 DRUG LABEL: Germa Ubre Mastitis
NDC: 73635-5807 | Form: OINTMENT
Manufacturer: Germa Products, LLC
Category: otc | Type: HUMAN OTC DRUG LABEL
Date: 20251010

ACTIVE INGREDIENTS: METHYL SALICYLATE 20 mg/1 mL
INACTIVE INGREDIENTS: WHITE PETROLATUM; D&C BROWN NO. 1; LANOLIN OIL; CAMPHOR (SYNTHETIC); ICHTHAMMOL

Ubre Mastitis Ointment

Active Ingredient

Methyl Salicylate 2%

Uses

Temporary relief of minor pain n joint & muscular aches n strains & sprain n backache.

Do not use, if prone to allergic reaction from any of the ingredients.

Do not use n on children • on irritated skin • in or near eyes or mucous membranes • on wounds or damaged skin.

Purpose

Topical Analgesic

Warnings

For external use only

Do not use on large areas of the body. • if you are taking any other medication or drinking alcohol • if safety seal is torn, broken or missing.

Warnings

KEEP OUT OF THE REACH OF CHILDREN

In case of accidental ingestion, get help or contact a Poison Control Center immediately.
Do not use • on children • on irritated skin • in or near eyes or mucous membranes • on wounds or damaged skin n if prone to allergic reaction from any of the ingredient n on large areas of the body. • if you are taking any other medication or drinking alcohol • if safety seal is torn, broken or missing.

PREGNANCY OR BREAST FEEDING

If pregnant or breast-feeding, ask a health professional before use.

Stop use and ask a doctor n if condition worsens or cleans up and occurs again n if symptoms persist for more than 7 days or irritation or severe burning occurs.

Other Information

Store at controlled room temperature 15-30ºC (59-86ºF)

Directions

Adults and children 12 years and older; apply to the affected area • no more than 3 to 4 times daily n children under 12 years of age; ask a Doctor.

Inactive Ingredients

Camphor crystals, D&C Brown #1, Lanolin, Ichthammol, and white petrolatum.